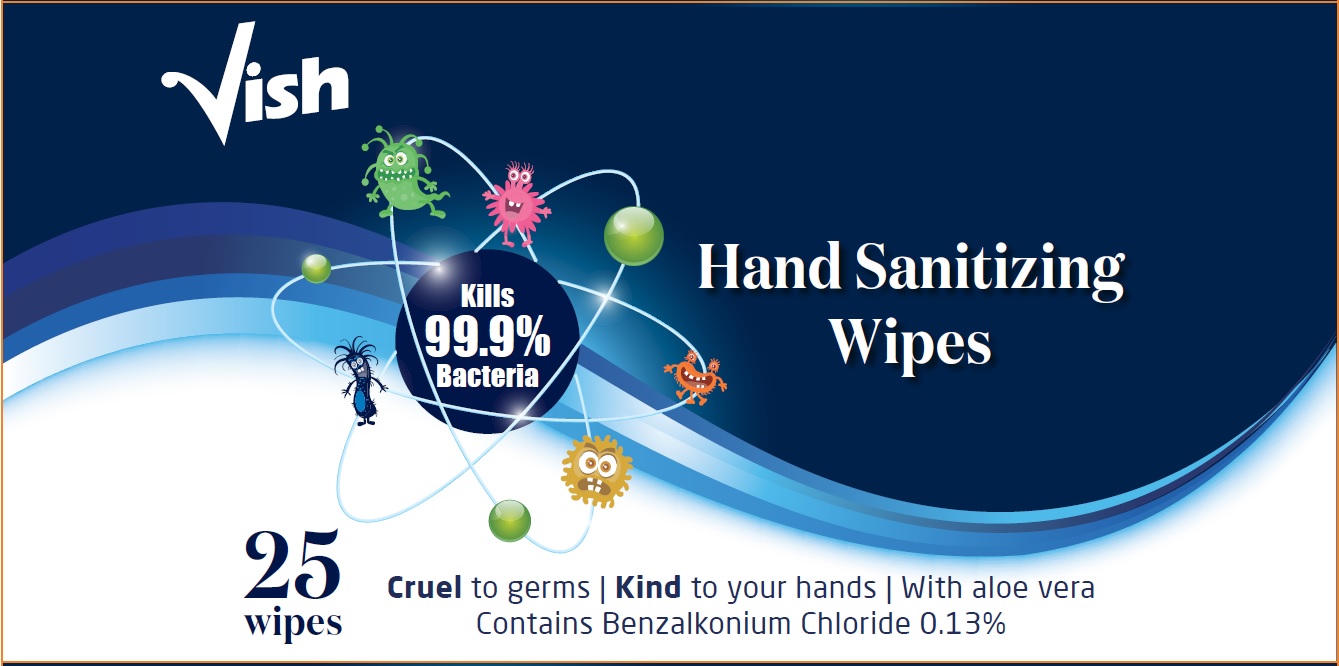 DRUG LABEL: Hand Sanitizing Wipes
NDC: 62685-219 | Form: CLOTH
Manufacturer: Tropical Degil Cosmetics Industries LTD
Category: otc | Type: HUMAN OTC DRUG LABEL
Date: 20201012

ACTIVE INGREDIENTS: BENZALKONIUM CHLORIDE 0.1755 g/135 g
INACTIVE INGREDIENTS: CITRIC ACID MONOHYDRATE; GLYCERIN; ALOE VERA LEAF; EDETATE DISODIUM; ALCOHOL; DEHYDROACETIC ACID; CAPRYLYL/CAPRYL OLIGOGLUCOSIDE; BENZOIC ACID; PHENOXYETHANOL; POLYSORBATE 20; WATER

Vish Hand Wipes

Active ingredient

Benzalkonium Chloride 0.13% v/v

Purpose

Hand Sanitizer, Antiseptic

Use

Hand sanitizer to help reduce bacteria on the skin.

Warnings

For external use only

Do not use

if you are allergic to any of the ingredients

When using this product do not use in or near the eyes. If contact occurs, rinse thoroughly with water.

Stop use and ask a doctor if irritation or redness develops and lasts for more than 72 hours.

Keep out of reach of children. If swallowed, get medical help or contact a Poison Control Center right away.

Directions

For adults and children 3 years and over, wipe hands and discard. Allow hands to air dry.

Inactive ingredients

Alcohol Denatured, Aloe Barbadensis Leaf Extract, Benzoic Acid, Caprylyl/Capryl Glucoside, Citric Acid, Dehydroacetic Acid, Disodium EDTA, Fragrance, Glycerin, Phenoxyethanol, Polysorbate 20, Water

Other information Store in a cool dry place.

Principal Display Panel

25 wipes. 0.13% Benzalkonium Chloride